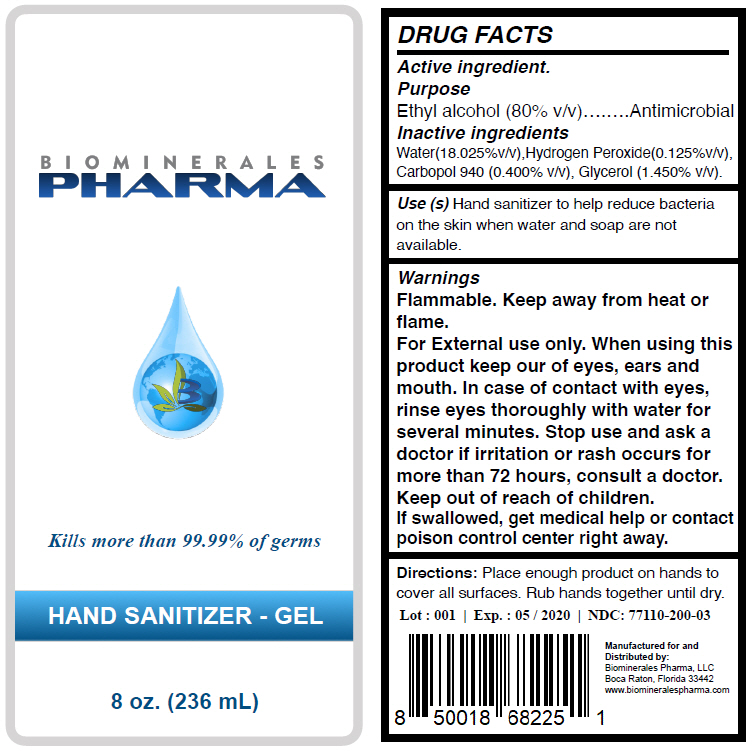 DRUG LABEL: HAND SANITIZER
NDC: 77110-200 | Form: GEL
Manufacturer: Biominerales Pharma, LLC
Category: otc | Type: HUMAN OTC DRUG LABEL
Date: 20200527

ACTIVE INGREDIENTS: Alcohol 80 mL/100 mL
INACTIVE INGREDIENTS: Water 18.025 mL/100 mL; Hydrogen Peroxide 0.125 mL/100 mL; CARBOMER HOMOPOLYMER TYPE C (ALLYL PENTAERYTHRITOL CROSSLINKED) 0.4 mL/100 mL; GLYCERIN 1.45 mL/100 mL

HAND SANITIZER

DRUG FACTS

Active ingredient

Ethyl alcohol (80% v/v)

Purpose

Antimicrobial

Inactive ingredients

Water(18.025%v/v),Hydrogen Peroxide(0.125%v/v), Carbopol 940 (0.400% v/v), Glycerol (1.450% v/v).

Use (s)

Hand sanitizer to help reduce bacteria on the skin when water and soap are not available.

Warnings

Flammable. Keep away from heat or flame.

For External use only. When using this product keep our of eyes, ears and mouth. In case of contact with eyes, rinse eyes thoroughly with water for several minutes. Stop use and ask a doctor if irritation or rash occurs for more than 72 hours, consult a doctor.

Keep out of reach of children. If swallowed, get medical help or contact poison control center right away.

Directions

Place enough product on hands to cover all surfaces. Rub hands together until dry.

Lot : 001 | Exp. : 05 / 2020 | NDC: 77110-200-03

Manufactured for and
Distributed by:
Biominerales Pharma, LLC
Boca Raton, Florida 33442

PRINCIPAL DISPLAY PANEL - 236 mL Bottle Label

BIOMINERALES
PHARMA

Kills more than 99.99% of germs

HAND SANITIZER - GEL

8 oz. (236 mL)